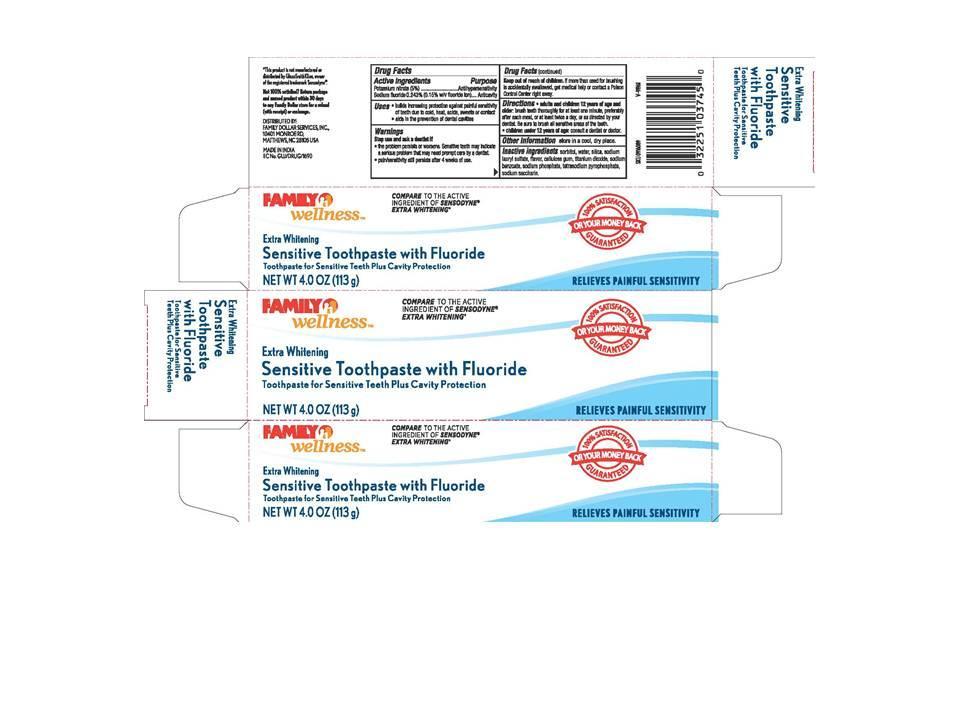 DRUG LABEL: Family Wellness Sensitive Extra Whitening
NDC: 55319-900 | Form: PASTE
Manufacturer: Family Wellness
Category: otc | Type: HUMAN OTC DRUG LABEL
Date: 20130411

ACTIVE INGREDIENTS: POTASSIUM NITRATE 5 mg/1 g; SODIUM FLUORIDE 1.5 mg/1 g
INACTIVE INGREDIENTS: SORBITOL; WATER; SODIUM LAURYL SULFATE; TITANIUM DIOXIDE; SODIUM BENZOATE; SODIUM PHOSPHATE; SACCHARIN SODIUM

Family Wellness Sensitive Extra Whitening

Active Ingredients

Potassium nitrate 5%........................................... Antihypersensitivity

Sodium Fluoride 0.243% (0.15% w/v fluoride ion).... Anticavity toothpaste

USES

- Builds increasing protection against painful sensitivity of teeth due to cold, heat, acids, sweets or contact
- Aids in the prevention of dental cavities

Purpose

- Builds increasing protection against painful sensitivity of teeh due to cold, heat, acids, sweets or contact
- Aids in the prevention of dental cavities

Stop use and ask a dentist if

- the problem persists or worsens. Sensitive teeth may indicate a serious problem that may need prompt care by a dentist.
- pain/sensitivity still persists after 4 weeks of use.

Keep out of reach of children

If more than used for brushing is accidentally swallowed, get medical help or contact a Poison Control Center right away.

Directions

Adults and children 12 years and older Brush teeth for at least one minute, preferably after each meal, or at least twice a day or as directed by your dentist. Be sure to brush sensitive areas of the teeth.
Children under 12 years of age Consult a dentist or doctor
Other information Store in a cool, dry place.

Inactive ingredients

sorbitol, water, silica, sodium lauryl sulfate, flavor, cellulose gum, titanium dioxide, sodium benzoate, sodium phosphate, tetrasodium pyrophosphate, sodium saccharin.